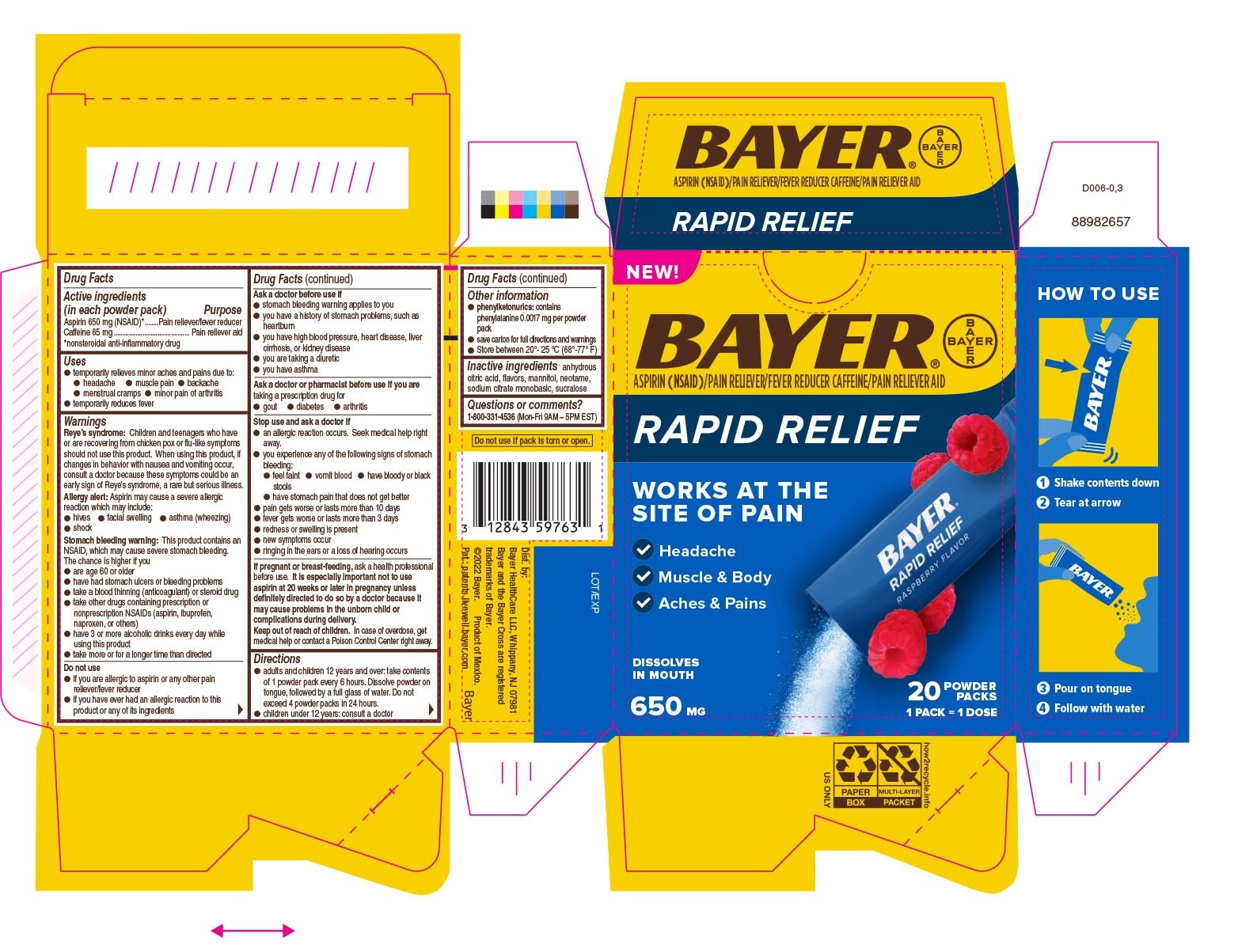 DRUG LABEL: Bayer Rapid Relief
NDC: 0280-0103 | Form: POWDER
Manufacturer: Bayer HealthCare LLC.
Category: otc | Type: HUMAN OTC DRUG LABEL
Date: 20251205

ACTIVE INGREDIENTS: CAFFEINE 65 mg/1 1; ASPIRIN 650 mg/1 1
INACTIVE INGREDIENTS: SUCRALOSE; ANHYDROUS CITRIC ACID; MANNITOL; NEOTAME; MONOSODIUM CITRATE

Bayer® Rapid Relief

Drug Facts

Active ingredient (in each tablet)

Aspirin 650 mg (NSAID)*

Caffeine 65 mg

*nonsteroidal anti-inflammatory drug

Purpose

Pain reliever/fever reducer

Pain reliever aid

Uses

temporarily relieves minor aches and pains due to: • headache • muscle pain • backache • menstrual cramps • minor pain of arthritis • temporarily reduces feve

Warnings

Reye’s syndrome: Children and teenagers who have or are recovering from chicken pox or flu-like symptoms should not use this product. When using this product, if changes in behavior with nausea and vomiting occur, consult a doctor because these symptoms could be an early sign of Reye’s syndrome, a rare but serious illness.

Allergy alert: Aspirin may cause a severe allergic reaction which may include: • hives • facial swelling • asthma (wheezing) • shock Stomach bleeding warning: This product contains an NSAID, which may cause severe stomach bleeding. The chance is higher if you ● are age 60 or older ● have had stomach ulcers or bleeding problems ● take a blood thinning (anticoagulant) or steroid drug ● take other drugs containing prescription or nonprescription NSAIDs (aspirin, ibuprofen, naproxen, or others) ● have 3 or more alcoholic drinks every day while using this product ● take more or for a longer time than directed

Do not use ● if you are allergic to aspirin or any other pain reliever/fever reducer ● if you have ever had an allergic reaction to this product or any of its Ingredients Ask a doctor before use if ● stomach bleeding warning applies to you ● you have a history of stomach problems, such as heartburn ● you have high blood pressure, heart disease, liver cirrhosis, or kidney disease ● you are taking a diuretic ● you have asthma Ask a doctor or pharmacist before use if you are taking a prescription drug for ● gout ● diabetes ● arthritis Stop use and ask a doctor if ● an allergic reaction occurs. Seek medical help right away. ● you experience any of the following signs of stomach bleeding: ● feel faint ● vomit blood ● have bloody or black stools ● have stomach pain that does not get better ● pain gets worse or lasts more than 10 days ● fever gets worse or lasts more than 3 days ● redness or swelling is present ● new symptoms occur ● ringing in the ears or a loss of hearing occurs If pregnant or breast-feeding, ask a health professional before use. It is especially important not to use aspirin at 20 weeks or later in pregnancy unless definitely directed to do so by a doctor because it may cause problems in the unborn child or complications during delivery.

Keep out of reach of children. In case of overdose, get medical help or contact a Poison Control Center right away.

Directions

adults and children 12 years and over: take contents of 1 powder pack every 6 hours. Dissolve powder on tongue, followed by a full glass of water. Do not exceed 4 powder packs in 24 hours. ● children under 12 years: consult a doctor

Other information

● phenylketonurics: contains phenylalanine 0.0017 mg per powder pack ● save carton for full directions and warnings ● Store between 20°- 25 °C (68°-77° F)

Inactive Ingredients

anhydrous citric acid, flavors, mannitol, neotame, sodium citrate monobasic, sucralose

Questions or comments?

1-800-331-4536 (Mon-Fri 9AM - 5PMEST)